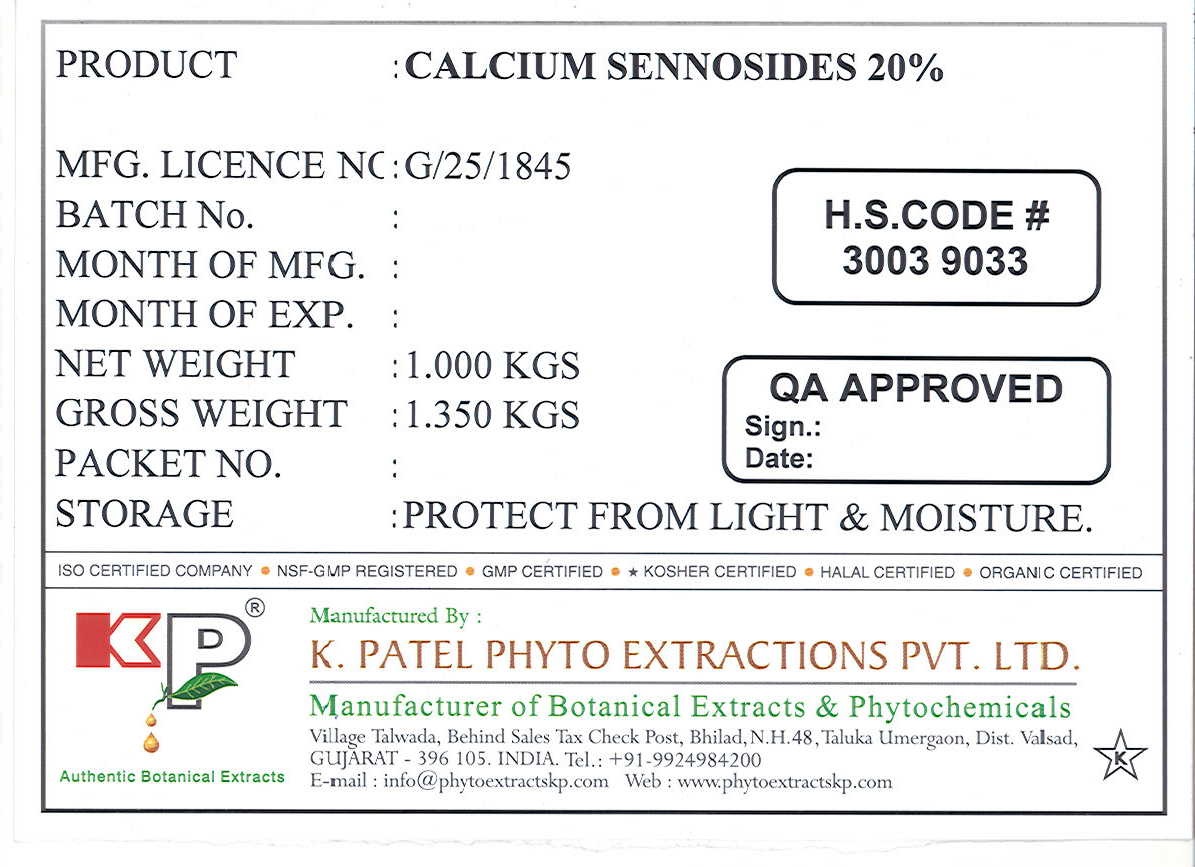 DRUG LABEL: Calcium Sennosides
NDC: 73276-001 | Form: POWDER
Manufacturer: K. Patel Phyto Extractions Private Limited
Category: other | Type: BULK INGREDIENT
Date: 20230110

ACTIVE INGREDIENTS: SENNOSIDES 1 kg/1 kg

Calcium Sennosides 20%